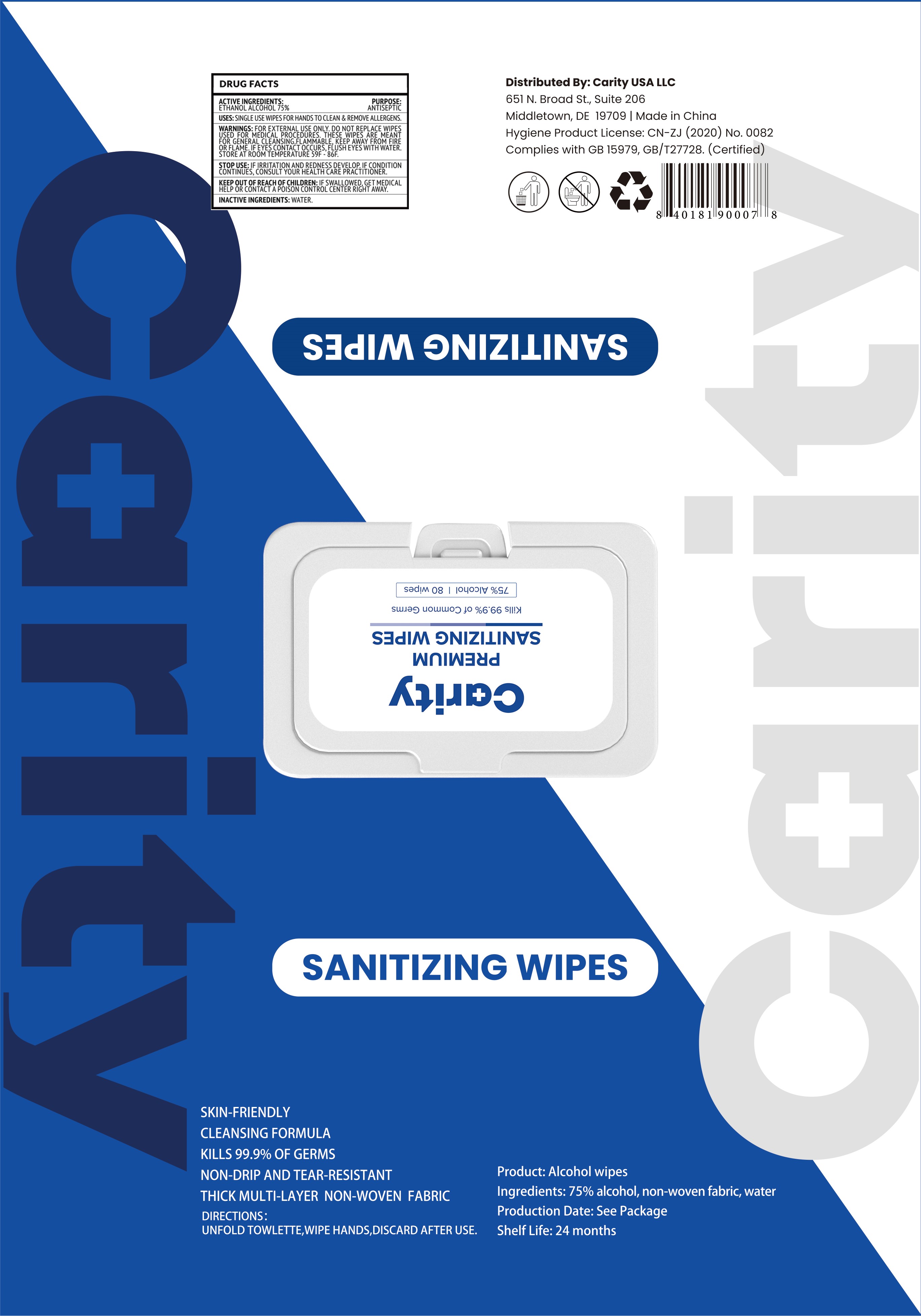 DRUG LABEL: ALCOHOL WIPES
NDC: 75163-080 | Form: CLOTH
Manufacturer: Zhuji Jianhe Paper Co., Ltd
Category: otc | Type: HUMAN OTC DRUG LABEL
Date: 20200816

ACTIVE INGREDIENTS: ALCOHOL 3.5 mL/1 1
INACTIVE INGREDIENTS: WATER

75163-080 ALCOHOL WIPES SANITIZING WIPES 3.5ml

Active Ingredient(s)

ETHANOL Alcohol 75% v/v. Purpose: Antiseptic

Use

SINGLE USE WIPES FOR HANDS TO CLEAN & REMOVE ALLERGENS.

Warnings

Do not apply this product to red and swollen skin, wound or any part sensitive to it.

Keep this product out of children’s reach in case they might eat it.
Alcohol is violatile, please use it as soon as possible after opening, store it in a cool and dry place, avoid direct sunlight and open fire, and avoid contact with eyes and damaged skin.

STOP USE

IF IRRITATION AND REDNESS DEVELOP. IF CONDITION CONTINUES, CONSULT YOUR HEALTH CARE PRACTITIONER.

Keep out of reach of children: IF SWALLOWED, GET MEDICAL HELP FOR CONTACT A POISON CONTROL CENTER RIGHT AWAY.

Inactive ingredients

Water

Purpose

ANTISEPTIC

WHEN USING

This product is used to wipe hands.

Do not use

- on children less than 2 months of age.
- on open skin wounds.

Directions

UNFOLD TOWLETTE, WIPE HANDS, DISCARD AFTER USE.

Other information

- Store between 15-30C (59-86F)
- Avoid freezing and excessive heat above 40C (104F)
- Shelf Life:24 months
- SKIN-FRENDLY
- CLEANSING FORMULA
- KILLS 99.9% OF GERMS
  - NON-DRIP AND TEAR-RESISTANT
  - THICK MULTI-LAYER NON-WOVEN FABRIC

Package Label - Principal Display Panel

80 CLOTH IN 1 BAG NDC:75163-080-80